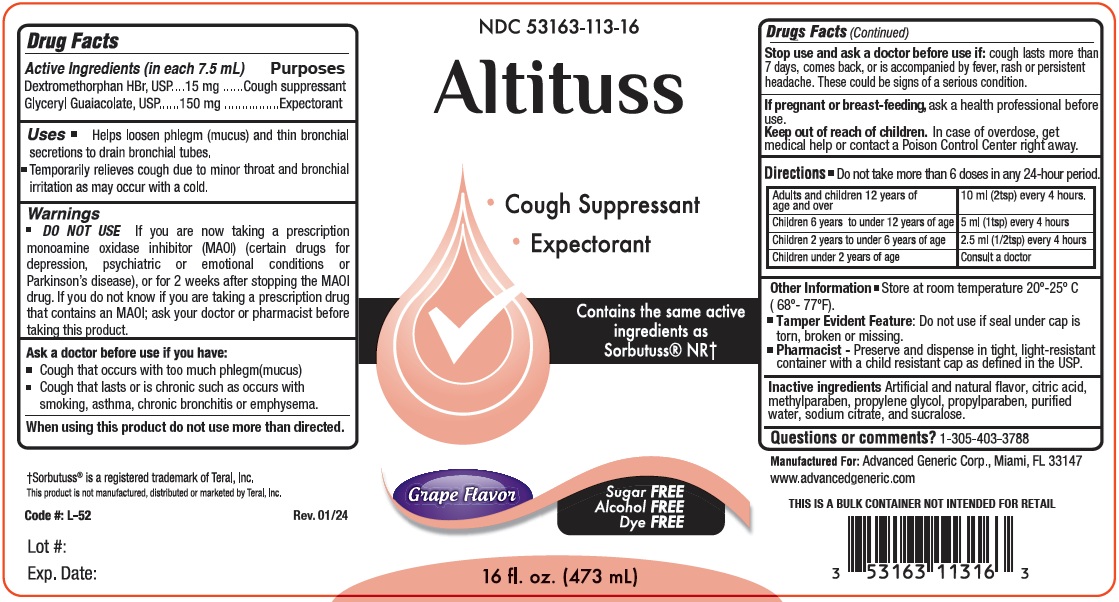 DRUG LABEL: Altituss
NDC: 53163-113 | Form: LIQUID
Manufacturer: Alternative Pharmacal Corporation
Category: otc | Type: HUMAN OTC DRUG LABEL
Date: 20251230

ACTIVE INGREDIENTS: DEXTROMETHORPHAN HYDROBROMIDE 15 mg/7.5 mL; GUAIFENESIN 150 mg/7.5 mL
INACTIVE INGREDIENTS: ANHYDROUS CITRIC ACID; METHYLPARABEN; PROPYLENE GLYCOL; PROPYLPARABEN; WATER; SODIUM CITRATE; SUCRALOSE

Alt-Altituss 113

Active Ingredients (in each 7.5 mL) Purpose

Dextromethorphan HBr.............. 15 mg ........ Cough suppressant

Glyceryl Guaiacolate .................. 150 mg ...... Expectorant

Purpose

Cough suppressant

Expectorant

Uses

Helps loosen phlegm (mucus) and thin bronchial secretions to drain bronchial tubes. Temporarily relieves cough due to minor throat and bronchial irritation as may occur with a cold.

Warnings

DO NOT USE

If you are now taking a prescription monoamine oxidase inhibitor (MAOI) (certain drugs for depression, psychiatric or emotional conditions or Parkinson's disease), or for 2 weeks after stopping the MAOI drug. If you do not know if you are taking a prescription drug that contains MAOI; ask your doctor or pharmacist before taking this product.

Ask a doctor before use if you have:

Cough that occurs with too much phlegm (mucus)

Cough that lasts or is chronic such as occurs with smoking, asthma, chronic bronchitis or emphysema

When using this product do not use more than directed.

Stop use and ask a doctor before use if: cough lasts more than 7 days, comes back, or is accompanied by fever, rash or persistent headache. These could be signs of a serious condition.

PREGNANCY OR BREAST FEEDING

If pregnant or breast-feeding, ask a health profession before use.

Keep out of reach of children. In case of overdose, get medical help or contact a Poison Control Center right away.

DOSAGE AND ADMINISTRATION

Directions Do not take more than 6 doses in any 24-hour period.

Adults and children 12 years of age and over | 10 ml (2tsp) every 4 hours
Children 6 years to under 12 years of age | 5 ml (1tsp) every 4 hours
Children 2 years to under 6 years of age | 2.5 ml (1/2 tsp) every 4 hours
Children under 2 years | Consult a doctor

INACTIVE INGREDIENT

Inactiveingredients

Artificial and Natural flavor, Citric acid, methylparaben, propylene glycol, propylparaben, purified water, sodium citrate, and sucralose

Questions or comments? 1-305-403-3788